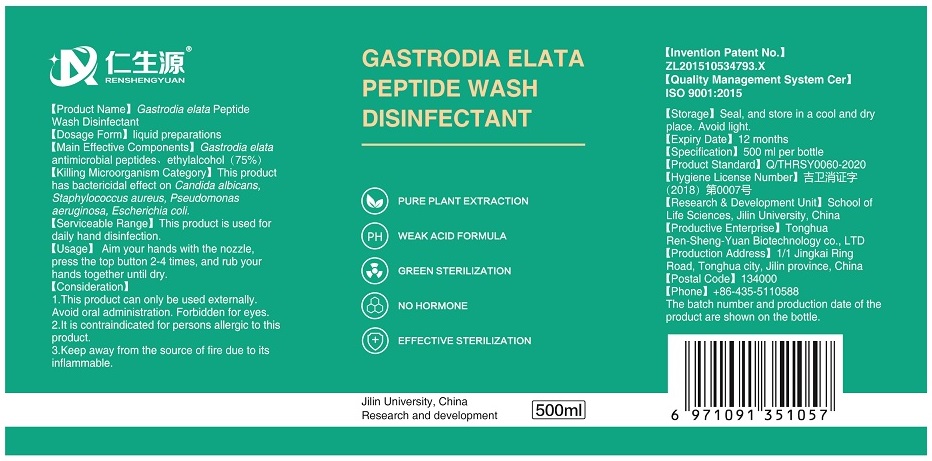 DRUG LABEL: Gastrodia elata Peptide Wash Disinfectant
NDC: 75449-1031 | Form: LIQUID
Manufacturer: Tonghua Ren-Sheng-Yuan Biotechnology Co., Ltd
Category: otc | Type: HUMAN OTC DRUG LABEL
Date: 20200424

ACTIVE INGREDIENTS: GASTRODIA ELATA WHOLE 27.5 g/500 mL; ALCOHOL 375 mL/500 mL
INACTIVE INGREDIENTS: GLYCERIN; WATER

RenShengYuan, 75% Ethanol, Wash Disinfectant, Liquid, 500mL

Active Ingredient(s)

Alcohol 75% v/v. Purpose: Antiseptic.

Gastrodia elata Blume peptide 5.5% v/v. Purpose: bactericidal against Candida albicans, Staphylococcus aureus, Pseudomonas aeruginosa, Escherichia coli.

Purpose

Antiseptic, Hand Sanitizer

Use

Hand Sanitizer to help reduce bacteria that potentially can cause disease. For use when soap and water are not available.

Used for daily hand disinfection.

Warnings

1. External use of disinfection gel. Ban on oral. Keep this container out of the reach of children.
2. Avoid use with antagonistic drugs.
3. Caution for allergic people.
4. Keep away from the source of fire due to its inflammable.
5. Seal, and store in a cool and dry place.

Do not use

- on children less than 2 months of age
- on open skin wounds
- in the eyes. in case of contact, rinse eyes thoroughly with water

When using this product keep out of eyes, ears, and mouth.

In case of contact with eyes, rinse eyes thoroughly with water.

Stop use and ask a doctor if irritation and redness develop and persist for more than 72 hours.

Keep out of reach of children. If swallowed, get medical help or contact a Poison Control Center right away.

Directions

Aim your hands with the nozzle, press the top button 2-4 times, and rub your hands together until dry.

Other information

Seal, and store in a cool and dry place.

Inactive ingredients

Water, Glycerine.